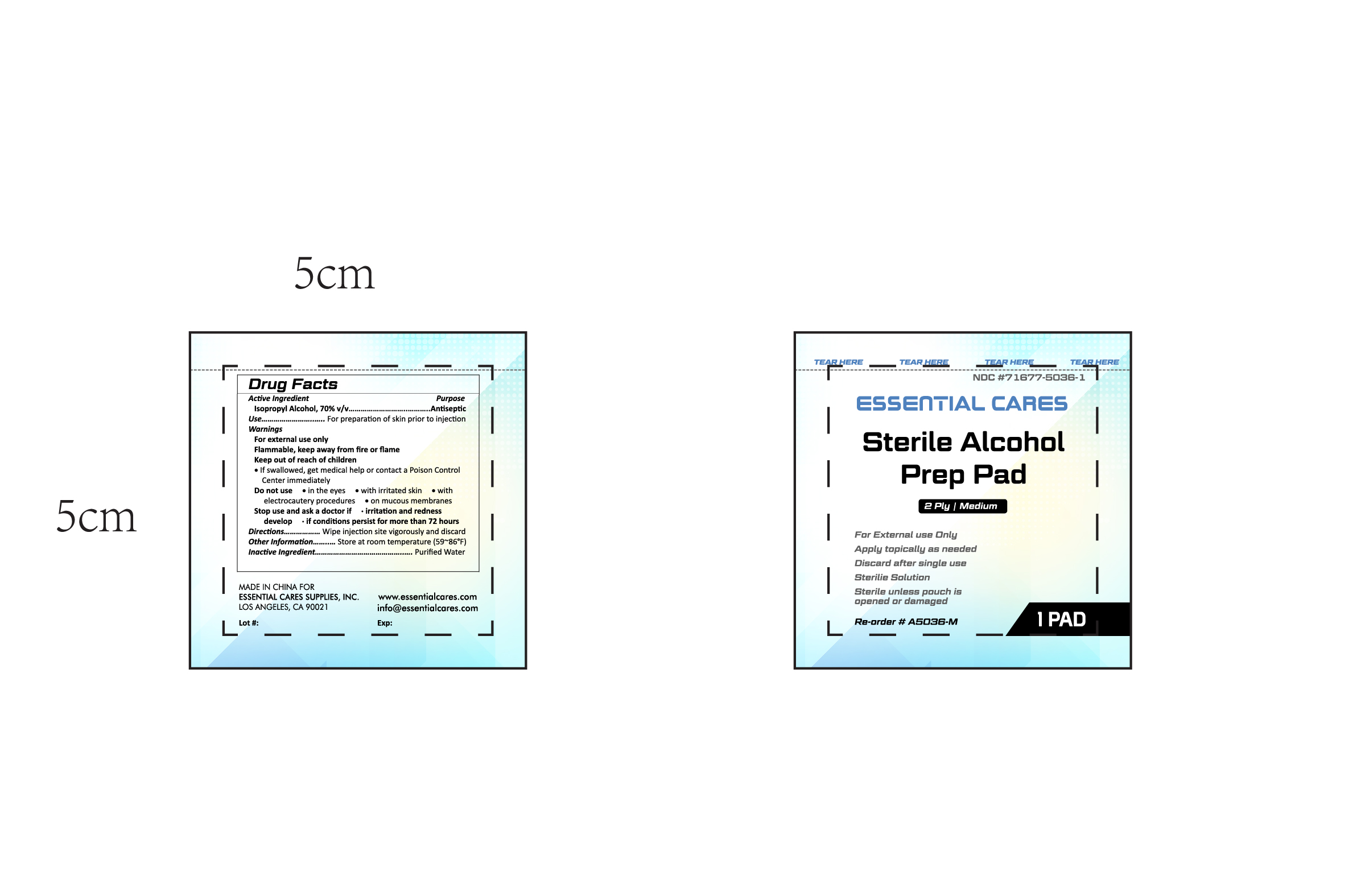 DRUG LABEL: Alcohol Prep Pads - Sterile
NDC: 71677-5036 | Form: SWAB
Manufacturer: Essential Cares Supplies, Inc.
Category: otc | Type: HUMAN OTC DRUG LABEL
Date: 20251003

ACTIVE INGREDIENTS: ISOPROPYL ALCOHOL 0.7 mL/1 mL
INACTIVE INGREDIENTS: WATER 1 mL/1 mL

Alcohol Prep Pads - Sterile

Active Ingredient

Active Ingredient Purpose

Isopropyl Alcohol, 70% v/v Antiseptic

Use

For preparation of skin prior to injection

Use

For preparation of skin prior to injection

Warnings

For External Use Only

Flammable, keep away from fire and flame

Keep out of reach of children

If swallowed, get medical help or contact a Poison Control Center immediately

Do not use

When irritation and redness develop

1) in the eyes, 2) with irritated skin, 3) with electrocautery procedures, 4) on mucous membranes

When irritation and redness develop

Ask a doctor if

Irritation and redness condtions persist for more than 72 hours

Directions

Wipe injection site vigorously and discard

Other information

Store at room temperature (59~86degrees F)

Inactive ingredient

Water